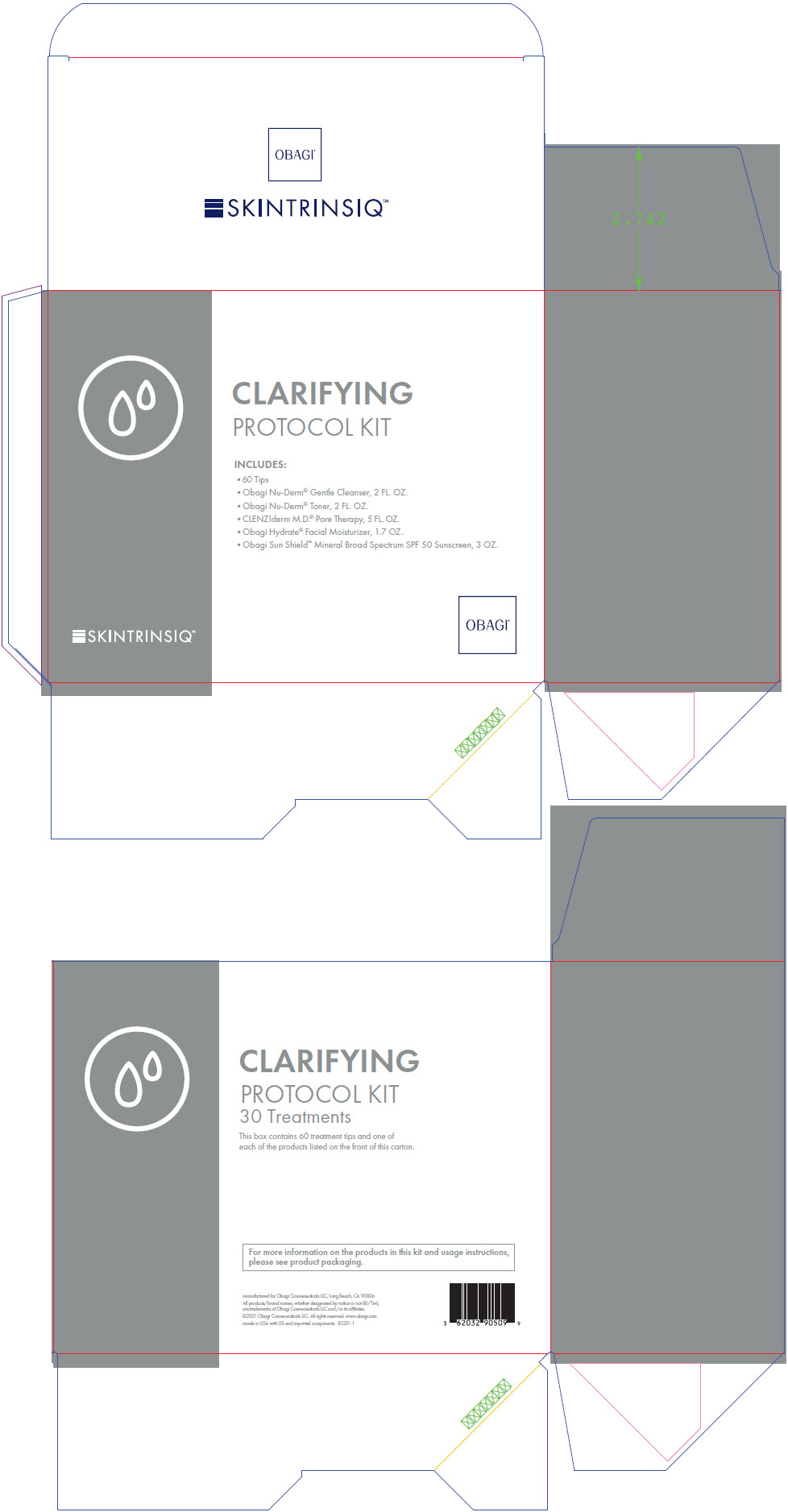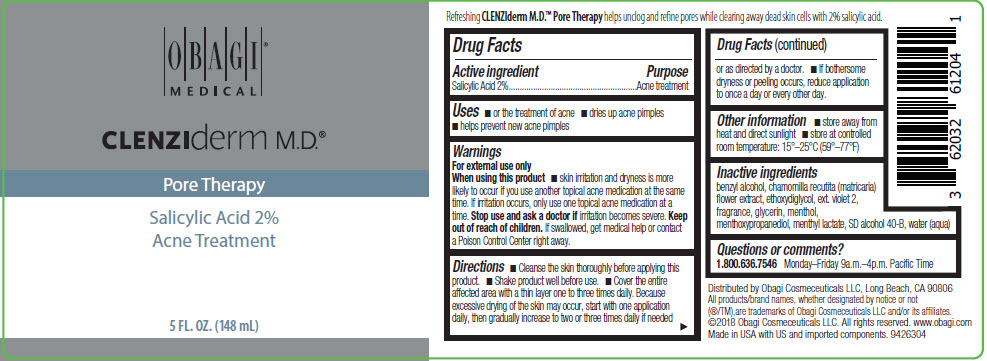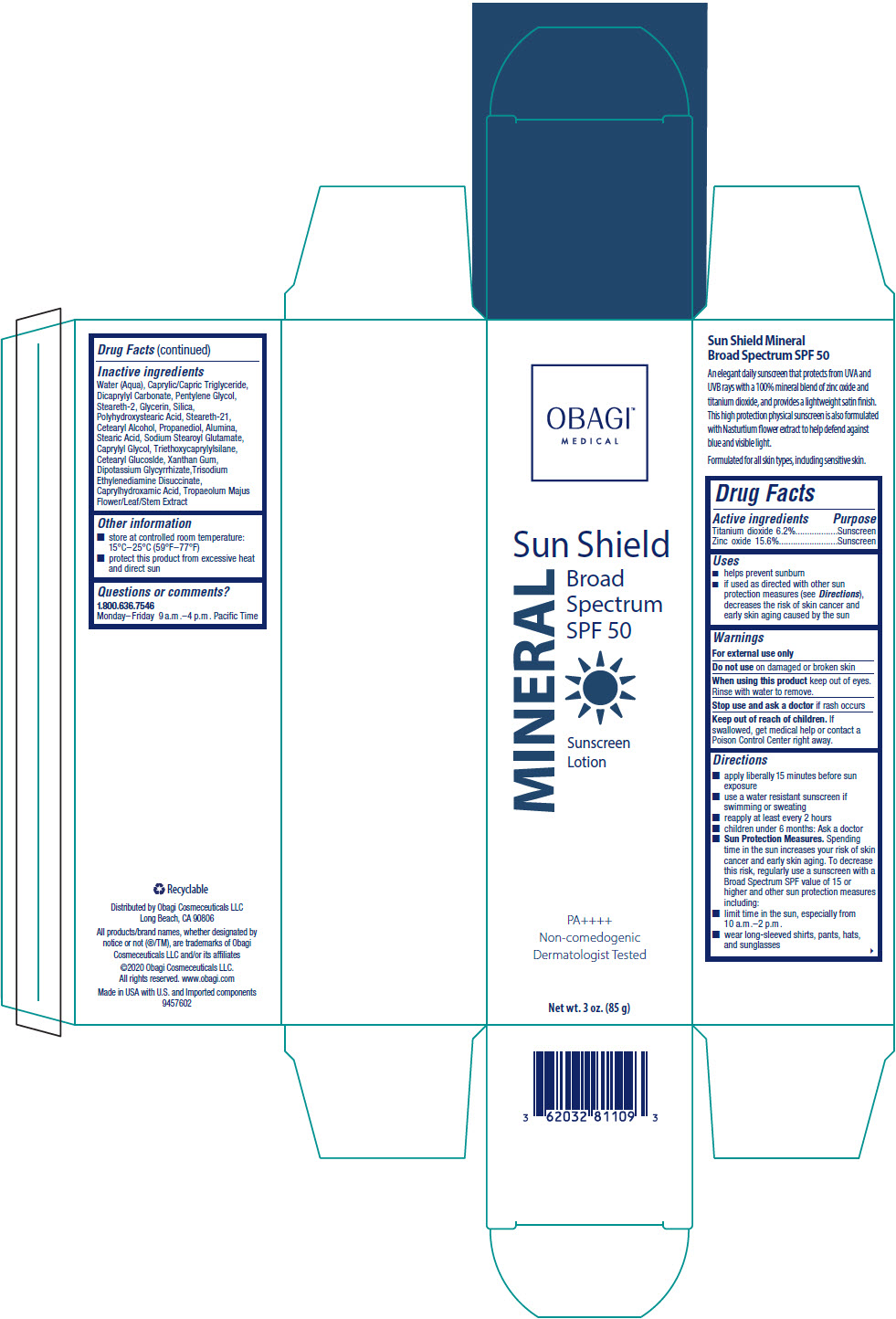 DRUG LABEL: Obagi Skintrinsiq Clarifiying Protocol
NDC: 62032-909 | Form: KIT | Route: TOPICAL
Manufacturer: Obagi Cosmeceuticals LLC
Category: otc | Type: HUMAN OTC DRUG LABEL
Date: 20250321

ACTIVE INGREDIENTS: SALICYLIC ACID 20 mg/1 mL; TITANIUM DIOXIDE 6.2 g/100 g; ZINC OXIDE 15.6 g/100 g
INACTIVE INGREDIENTS: 3-((L-MENTHYL)OXY)PROPANE-1,2-DIOL; ALCOHOL; BENZYL ALCOHOL; CHAMOMILE; DIETHYLENE GLYCOL MONOETHYL ETHER; EXT. D&C VIOLET NO. 2; GLYCERIN; MENTHOL, UNSPECIFIED FORM; MENTHYL LACTATE, (-)-; WATER; ALUMINUM OXIDE; CAPRYLHYDROXAMIC ACID; CAPRYLYL GLYCOL; CETEARYL GLUCOSIDE; CETOSTEARYL ALCOHOL; DICAPRYLYL CARBONATE; GLYCERIN; GLYCYRRHIZINATE DIPOTASSIUM; MEDIUM-CHAIN TRIGLYCERIDES; PENTYLENE GLYCOL; POLYHYDROXYSTEARIC ACID (2300 MW); PROPANEDIOL; SILICON DIOXIDE; SODIUM STEAROYL GLUTAMATE; STEARETH-2; STEARETH-21; STEARIC ACID; TRIETHOXYCAPRYLYLSILANE; TRISODIUM ETHYLENEDIAMINE DISUCCINATE; TROPAEOLUM MAJUS FLOWERING TOP; WATER; XANTHAN GUM

Obagi ® Skintrinsiq™ Clarifiying Protocol Kit

Obagi® Medical CLENZIderm M.D.® Pore Therapy

Drug Facts

Active ingredient

Salicylic Acid 2%

Purpose

Acne treatment

Uses

- or the treatment of acne
- dries up acne pimples
- helps prevent new acne pimples

Warnings

For external use only

When using this product

- skin irritation and dryness is more likely to occur if you use another topical acne medication at the same time. If irritation occurs, only use one topical acne medication at a time.

Stop use and ask a doctor if irritation becomes severe.

Keep out of reach of children. If swallowed, get medical help or contact a Poison Control Center right away.

Directions

- Cleanse the skin thoroughly before applying this product.
- Shake product well before use.
- Cover the entire affected area with a thin layer one to three times daily. Because excessive drying of the skin may occur, start with one application daily, then gradually increase to two or three times daily if needed or as directed by a doctor.
- If bothersome dryness or peeling occurs, reduce application to once a day or every other day.

Other information

- store away from heat and direct sunlight
- store at controlled room temperature: 15°–25°C (59°–77°F)

Inactive ingredients

benzyl alcohol, chamomilla recutita (matricaria) ﬂower extract, ethoxydiglycol, ext. violet 2, fragrance, glycerin, menthol, menthoxypropanediol, menthyl lactate, SD alcohol 40-B, water (aqua)

Questions or comments?

1.800.636.7546 Monday–Friday 9a.m.–4p.m. Paciﬁc Time

Distributed by Obagi Cosmeceuticals LLC, Long Beach, CA 90806

Obagi™ Sun Shield Mineral Broad Spectrum SPF 50 Sunscreen

Drug Facts

ACTIVE INGREDIENT

Active ingredients | Purpose
Titanium dioxide 6.2% | Sunscreen
Zinc oxide 15.6% | Sunscreen

Uses

- helps prevent sunburn
- if used as directed with other sun protection measures (see Directions), decreases the risk of skin cancer and early skin aging caused by the sun

Warnings

For external use only

Do not use on damaged or broken skin

When using this product keep out of eyes. Rinse with water to remove.

Stop use and ask doctor if rash occurs

Keep out of reach of children. If swallowed, get medical help or contact a Poison Control Center right away.

Directions

- apply liberally 15 minutes before sun exposure
- use a water resistant sunscreen if swimming or sweating
- reapply at least every 2 hours
- children under 6 months: Ask a doctor
- Sun Protection Measures. Spending time in the sun increases your risk of skin cancer and early skin aging. To decrease this risk, regularly use a sunscreen with a Broad Spectrum SPF value of 15 or higher and other sun protection measures including:
  - limit time in the sun, especially from 10 a.m.–2 p.m.
  - wear long-sleeved shirts, pants, hats, and sunglasses

Inactive ingredients

Water (Aqua), Caprylic/Capric Triglyceride, Dicaprylyl Carbonate, Pentylene Glycol, Steareth-2, Glycerin, Silica, Polyhydroxystearic Acid, Steareth-21, Cetearyl Alcohol, Propanediol, Alumina, Stearic Acid, Sodium Stearoyl Glutamate, Caprylyl Glycol, Triethoxycaprylylsilane, Cetearyl Glucoslde, Xanthan Gum, Dipotassium Glycyrrhizate,Trisodium Ethylenediamine Disuccinate, Caprylhydroxamic Acid, Tropaeolum Majus Flower/Leaf/Stem Extract

Other information

- store at controlled room temperature: 15°C–25°C (59°F–77°F)
- protect this product from excessive heat and direct sun

Questions or comments?

1.800.636.7546

Monday–Friday 9 a.m.–4 p.m. Paciﬁc Time

Distributed by Obagi Cosmeceuticals LLC
Long Beach, CA 90806

PRINCIPAL DISPLAY PANEL - Kit Carton

SKINTRINSIQ™

CLARIFYING
PROTOCOL KIT

INCLUDES:

- 60 Tips
- Obagi Nu-Derm® Gentle Cleanser, 2 FL. OZ.
- Obagi Nu-Derm® Toner, 2 FL. OZ.
- CLENZIderm M.D.® Pore Therapy, 5 FL. OZ.
- Obagi Hydrate® Facial Moisturizer, 1.7 OZ.
- Obagi Sun Shield™ Mineral Broad Spectrum SPF 50 Sunscreen, 3 OZ.

OBAGI®

PRINCIPAL DISPLAY PANEL - 148 mL Bottle Label

OBAGI®
MEDICAL

CLENZIderm M.D.®

Pore Therapy

Salicylic Acid 2%
Acne Treatment

5 FL. OZ. (148 mL)

PRINCIPAL DISPLAY PANEL - 85 g Tube Carton

OBAGI™
MEDICAL

Sun Shield
Broad
Spectrum
SPF 50

MINERAL

Sunscreen
Lotion

PA++++
Non-comedogenic
Dermatologist Tested

Net wt. 3 oz. (85 g)